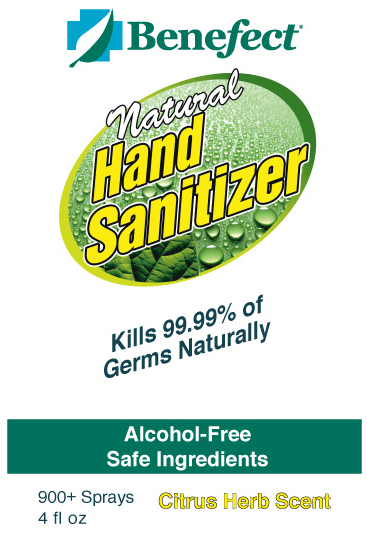 DRUG LABEL: Benefect Natural Hand Sanitizer
NDC: 51456-299 | Form: LIQUID
Manufacturer: Sensible Life Products
Category: otc | Type: HUMAN OTC DRUG LABEL
Date: 20100608

ACTIVE INGREDIENTS: Thymol .5 mL/1 L

Drug Facts

ACTIVE INGREDIENT

Benefect® Natural Hand Sanitizer is proven to kill 99.99%
of germs using only safe plant-based ingredients.
Drug Facts
Active Ingredient: Purpose
Thymus Vulgaris Oil (Thymol 0.05%)..........................Sanitizer
Use: Sanitize hands when you can’t wash with soap and water.
Warning: For external use only.
Instruct children on proper use.
Stop use and ask a doctor if skin becomes irritated.
Directions: Spray until hands are wet and rub thoroughly until dry.
Inactive Ingredients: Aloe Barbadensis (Aloe) Leaf Juice*, Citric
Acid, Citrus Aurantium Dulcis (Orange) Oil, Copper PCA*,
Hydrolyzed Oats*, Litsea Cubeba (Litsea) Oil, Origanum Vulgare
(Oregano) Oil, Sodium Citrate, Sodium Coco Sulfate, Sodium
Decylglucosides Hydroxypropyl Sulfonate, Water
*skin conditioners It’s About Thyme!TM
Sensible Life Products
7 Innovation Dr.
Ontario, CA
L9H 7H9
(905)690-7474
www.Benefect.com